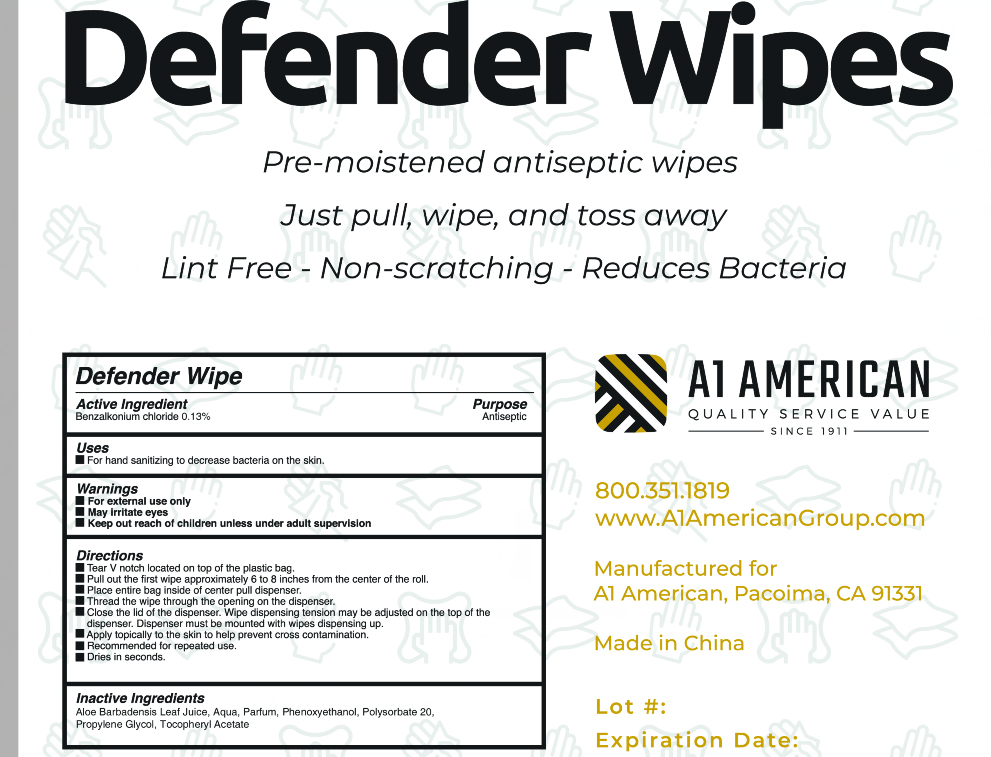 DRUG LABEL: Defender wipes
NDC: 79014-001 | Form: CLOTH
Manufacturer: Wenzhou Bofeng Packaging Co., Ltd.
Category: otc | Type: HUMAN OTC DRUG LABEL
Date: 20200615

ACTIVE INGREDIENTS: BENZALKONIUM CHLORIDE 0.13 g/100 g
INACTIVE INGREDIENTS: POLYSORBATE 20; ALPHA-TOCOPHEROL ACETATE; ALOE VERA LEAF; PHENOXYETHANOL; WATER; PROPYLENE GLYCOL

Defender wipes

Active Ingredient(s)

Benzalkonium chloride 0.13%. Purpose: Antiseptic

Purpose

Antiseptic

Use

For hand sanitizing to decrease bacteria on the skin.

Warnings

For external use only.

May irritate eyes

Keep out of reach of children unless under adult supervision.

STOP USE

May irritate eyes

Keep out of reach of children unless under adult supervision.

Directions

- Tear V notch located on top of the plastic bag.
- Pull out the first wipe approximately 6 to 8 inches from the center of the roll.
- Place entire bag inside of center pull dispenser.
- Close the lid of the dispenser. Wipe dispensing tension may be adjusted on the top of the dispenser. Dispenser must be mounted with wipes dispensing up.
- Apply topically to the skin to help prevent cross contamination.
- Recommended for repeated use.
- Dries in seconds.

Inactive ingredients

Aloe Barbadensis Leaf Juice, Aqua, Parfum, Phenoxyethanol, Polysorbate 20, Propylene Glycol, Tocopheryl Acetate.